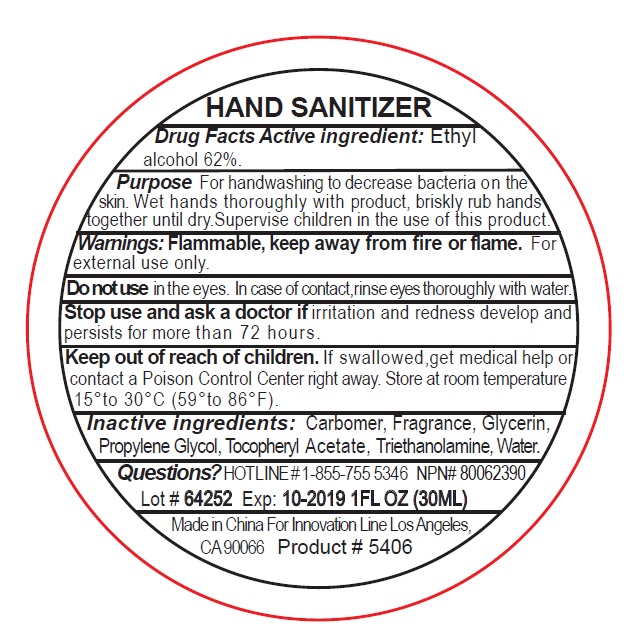 DRUG LABEL: 5406 hand sanitizer
NDC: 76138-116 | Form: GEL
Manufacturer: Innovation Specialties
Category: otc | Type: HUMAN OTC DRUG LABEL
Date: 20240710

ACTIVE INGREDIENTS: ALCOHOL 62 mL/100 mL
INACTIVE INGREDIENTS: CARBOMER HOMOPOLYMER, UNSPECIFIED TYPE; GLYCERIN; PROPYLENE GLYCOL; .ALPHA.-TOCOPHEROL ACETATE; TROLAMINE; WATER

5406 hand sanitizer

Active ingredient:Ethyl alcohol 62%.

Purpose:Antiseptic

INDICATIONS AND USAGE

For handwashing to decrease bacteria on the skin.

WARNINGS

Warnings:Flammable, keep away from fire or flame. For external use only.

Do not usein the eyes. In case of contact, rinse eyes thoroughly with water.

Stop use and ask a doctor ifirritation and redness develop and persists for more than 72 hours.

Keep out of reach of children. If swallowed, get medical help or contact a Poison Control Center right away.

DOSAGE AND ADMINISTRATION

Wet hands thoroughly with product, briskly rub hands together until dry. Supervise children in the use of this product.

INACTIVE INGREDIENT

Inactive ingredients:Carbomer, Fragrance, Glycerin, Propylene Glycol, Tocopheryl Acetate, Triethanolamine, Water.

Questions?HOTLINE # 1-855-755 5346 NPN# 80062390

STORAGE AND HANDLING

Store at room temperature 15° to 30°C (59° to 86°F).

Made in China For Innovation Line Los Angeles,
CA 90066 Product # 5406